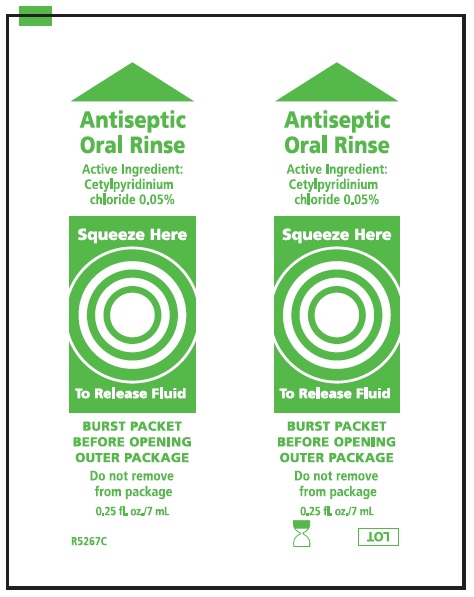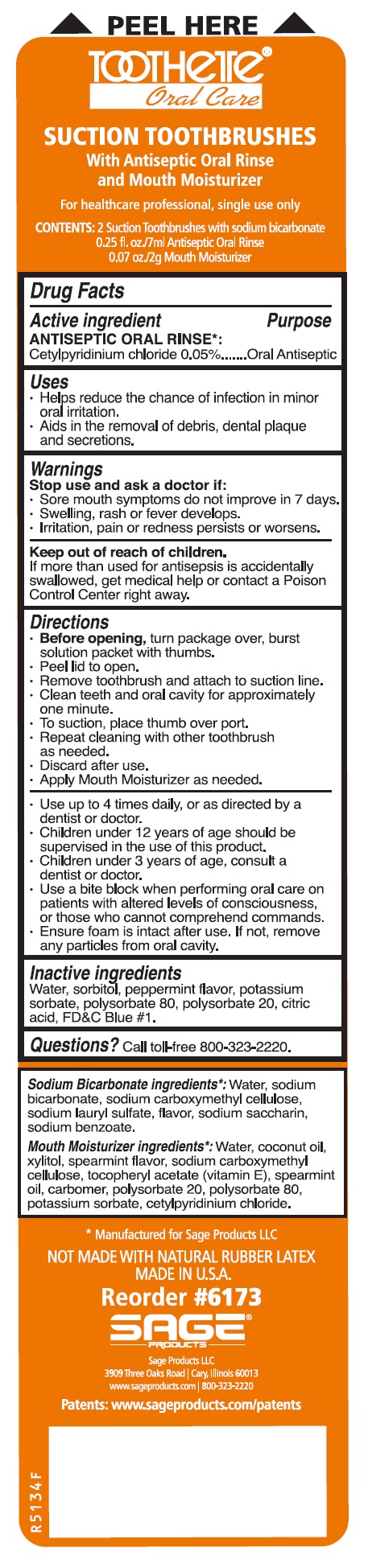 DRUG LABEL: Suction Toothbrushes
NDC: 53462-273 | Form: KIT | Route: BUCCAL
Manufacturer: Sage Products LLC
Category: otc | Type: HUMAN OTC DRUG LABEL
Date: 20180426

ACTIVE INGREDIENTS: CETYLPYRIDINIUM CHLORIDE 0.5 mg/1 mL
INACTIVE INGREDIENTS: WATER; SORBITOL; PEPPERMINT; POTASSIUM SORBATE; POLYSORBATE 80; POLYSORBATE 20; CITRIC ACID MONOHYDRATE; FD&C BLUE NO. 1

Suction Toothbrushes

Drug Facts

Active Ingredient | Purpose
Antiseptic Oral Rinse
.05% Cetylpyridinium chloride | Oral Antiseptic

Uses

- Helps reduce the chance of infection in minor oral irritation.
- Aids in the removal of debris, dental plaque and secretions.

Warnings

Stop use and ask a doctor if:

- Sore mouth symptoms do not improve in 7 days.
- Swelling, rash or fever develops.
- Irritation, pain or redness persists or worsens.

Keep out of reach of children.

If more than used for antisepsis is accidentally swallowed, get medical help or contact a Poison Control Center right away.

Directions

- Before opening, turn package over, burst solution packet with thumbs.
- Peel lid to open.
- Remove toothbrush and attach to suction line.
- Clean teeth and oral cavity for approximately one minute.
- To suction, place thumb over port.
- Repeat cleaning with other toothbrush as needed.
- Discard after use.
- Apply Mouth Moisturizer as needed.
- Use up to 4 times daily, or as directed by a dentist or doctor.
- Children under 12 years of age should be supervised in the use of this product.
- Children under 3 years of age, consult a dentist or doctor.
- Use a bite block when performing oral care on patients with altered levels of consciousness or those who cannot comprehend commands.
- Ensure foam is intact after use. If not, remove any particles from oral cavity.

Inactive Ingredients

Water, sorbitol, peppermint flavor, potssium sorbate, polysorbate 80, polysorbate 20, citric acid, FD&C Blue #1.

Questions

Call toll free 800-323-2220